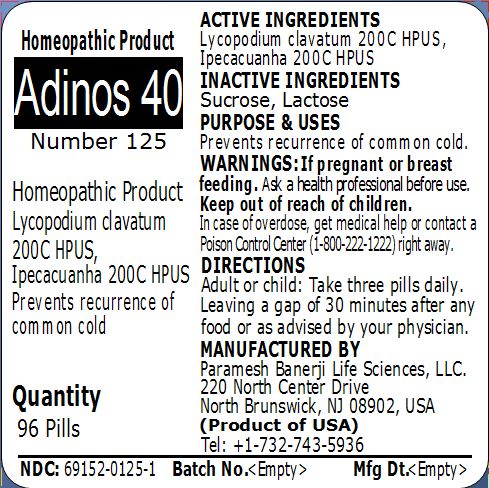 DRUG LABEL: Adinos 40 (Number 125)
NDC: 69152-0125 | Form: PELLET
Manufacturer: Paramesh Banerji Life Sciences LLC
Category: homeopathic | Type: HUMAN OTC DRUG LABEL
Date: 20150304

ACTIVE INGREDIENTS: LYCOPODIUM CLAVATUM SPORE 200 [hp_C]/1 1; IPECAC 200 [hp_C]/1 1
INACTIVE INGREDIENTS: LACTOSE; SUCROSE

Active Ingredients

Lycopodium clavatum 200C HPUS, Ipecacuanha 200C HPUS

Inactive Ingredients

Sucrose, Lactose

Purpose

Prevents recurrence of common cold

Uses

Prevents recurrence of common cold

Warnings

If pregnant or breast feeding ask a health professional before use.

Keep out of reach of children. In case of overdose, get medical help or contact a Poison Control Center (1-800-222-1222) right away.

Direction

Adult or child: Take three pills daily. Leaving a gap of 30 minutes after any food or as advised by your physician.

Manufactured by

Paramesh Banerji Life Sciences, LLC

220 North Center Drive

North Brunswick, NJ 08902, USA

Product of USA

Tel: +1-732-743-5936

Principal Display Panel

Homeopathic Product

Adinos 40

Number 125

Homeopathic Product

Lycopodium clavatum 200C HPUS, Ipecacuanha 200C HPUS

Prevents recurrence of common cold

Quantity

96 Pills